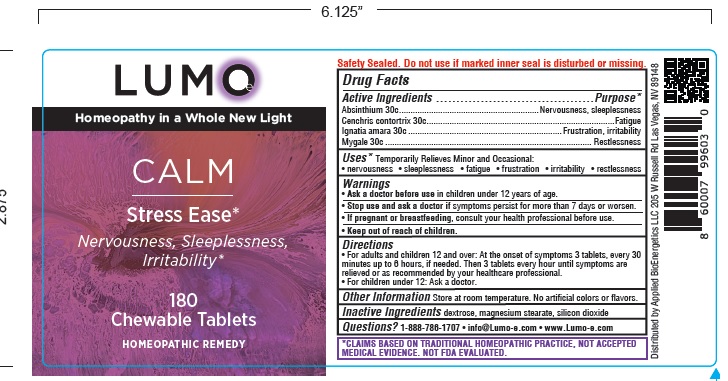 DRUG LABEL: LUMO Calm Stress Ease
NDC: 81425-001 | Form: TABLET, CHEWABLE
Manufacturer: Applied Bioenergetics, LLC
Category: homeopathic | Type: HUMAN OTC DRUG LABEL
Date: 20251110

ACTIVE INGREDIENTS: WORMWOOD 30 [hp_C]/1 1; AGKISTRODON CONTORTRIX VENOM 30 [hp_C]/1 1; STRYCHNOS IGNATII SEED 30 [hp_C]/1 1; AVICULARIA AVICULARIA 30 [hp_C]/1 1
INACTIVE INGREDIENTS: DEXTROSE; MAGNESIUM STEARATE; SILICON DIOXIDE

LUMO-e Calm Stress Ease

Drug Facts

Active Ingredients
Absinthium 30c
Cenchris contortrix 30c
Ignatia amara 30c
Mygale 30c

Purpose*
Absinthium ............................................................. Nervousness, sleeplessness
Cenchris contortrix ...................................................Fatigue
Ignatia amara ......................................................... Frustration, irritability
Mygale ................................................................... Restlessness

INDICATIONS AND USAGE

Uses* Temporarily Relieves Minor and Occasional:
• nervousness • sleeplessness • fatigue • frustration • irritability • restlessness

Warnings
• Ask a doctor before use in children under 12 years of age.
• Stop use and ask a doctor if symptoms persist for more than 7 days or worsen.
• If pregnant or breastfeeding, consult your health professional before use.

• Keep out of reach of children.

Directions
• For adults and children 12 and over: At the onset of symptoms 3 tablets, every 30
minutes up to 6 hours, if needed. Then 3 tablets every hour until symptoms are
relieved or as recommended by your healthcare professional.
• For children under 12: Ask a doctor.

Other Information Store at room temperature. No artificial colors or flavors.

Inactive Ingredients dextrose, magnesium stearate, silicon dioxide

QUESTIONS

Questions? 1-888-786-1707 • info@Lumo-e.com • www.Lumo-e.com

*CLAIMS BASED ON TRADITIONAL HOMEOPATHIC PRACTICE, NOT ACCEPTED
MEDICAL EVIDENCE. NOT FDA EVALUATED.

Product Label LUMO-e Calm

LUMO-e
Homeopathy in a Whole New Light

CALM

Stress Ease*
Nervousness, Sleeplessness,
Irritability*

180
Chewable Tablets

HOMEOPATHIC REMEDY

Safety Sealed. Do not use if marked inner seal is disturbed or missing.

*CLAIMS BASED ON TRADITIONAL HOMEOPATHIC PRACTICE, NOT ACCEPTED
MEDICAL EVIDENCE. NOT FDA EVALUATED.

Distributed by Applied BioEnergetics LLC 205 W Russell Rd Las Vegas, NV 89148

res